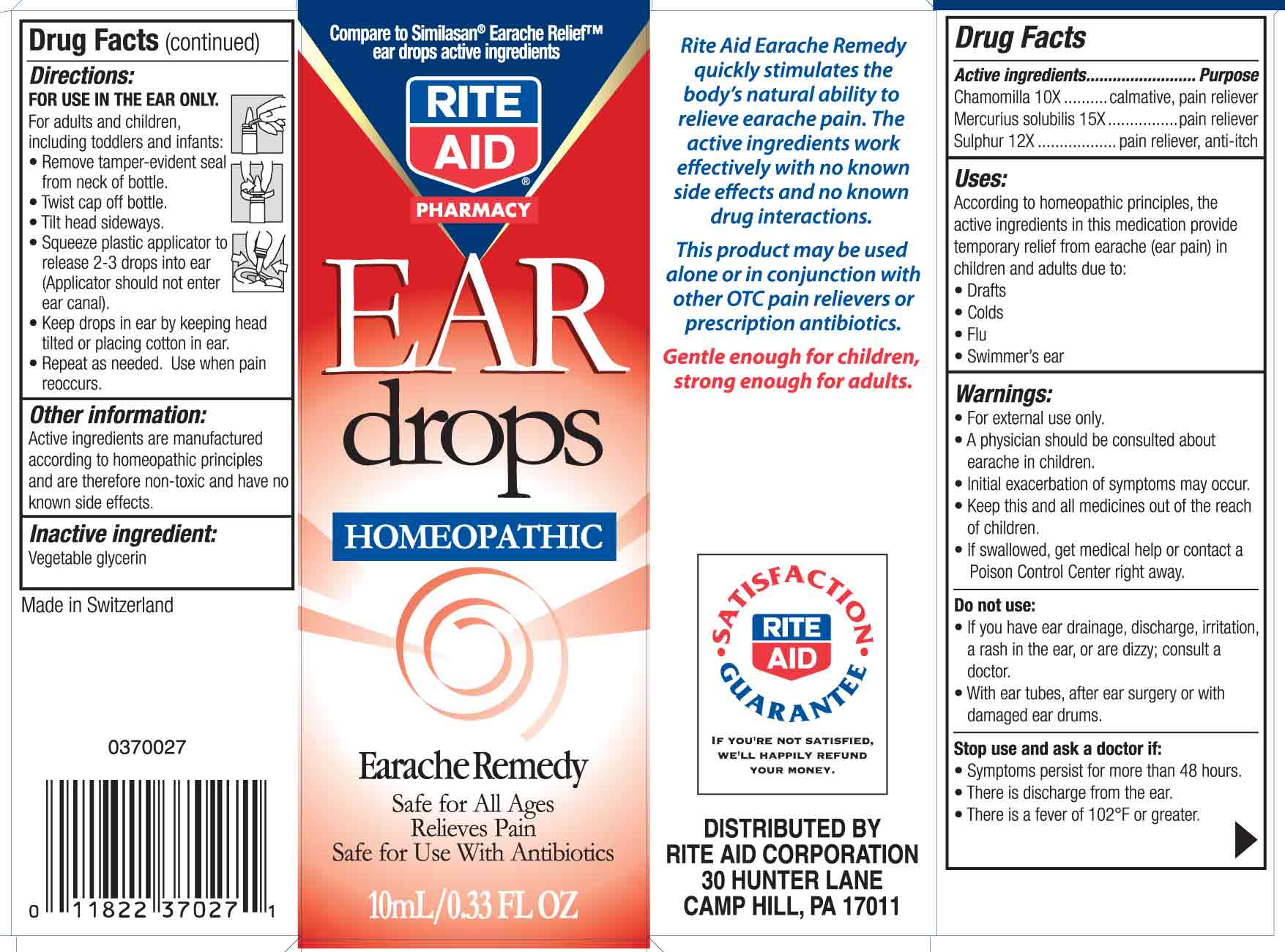 DRUG LABEL: Rite Aid Ear Drops
NDC: 11822-9002 | Form: SOLUTION
Manufacturer: Rite Aid Corporation
Category: homeopathic | Type: HUMAN OTC DRUG LABEL
Date: 20100825

ACTIVE INGREDIENTS: CHAMOMILE 10 [hp_X]/10 mL; MERCURIUS SOLUBILIS 15 [hp_X]/10 mL; SULFUR 12 [hp_X]/10 mL
INACTIVE INGREDIENTS: GLYCERIN

Rite Aid Ear Drops

Active ingredient

Chamomilla 10X

Purpose

calmative, pain reliever

Active ingredient

Mercurius solubilis 15X

Purpose

pain reliever

Active ingredient

Sulphur 12X

Purpose

pain reliever, anti-itch

Uses:

According to homeopathic principles, the active ingredinets in this medication provide temporary relief from earache (ear pain) in children and adults due to:
- Drafts
- Colds
- Flu
- Swimmer's ear

Warnings:

- For external use only
- A physician should be consulted about earache in children.
- Initial exacerbation of symptoms may occur.
- Keep this and all medicines out of the reach of children.
- If swallowed, get medical help or contact a Poison Control Center right away.

Keep out of reach of children

Keep this and all medicines out of the reach of children

Do not use:

- If you have ear drainage, discharge, irritation, a rash in the ear, or are dizzy; consult a doctor.
- With ear tubes, after ear surgery or with damaged ear drums.

Stop use and ask a doctor if:

- Symptoms persist for more than 48 hours.
- These is discharge from the ear.
- There is a fever of 102F or greater.

Directions:

FOR USE IN THE EAR ONLY
For adults and children, including toddlers and infants:
- Remove tamper-evident seal from neck of bottle.
- Twist cap off bottle.
- Tilt head sideways.
- Squeeze plastic applicator to release 2-3 drops into ear (applicator should not enter ear canal).
- Keep drops in ear by keeping head tilted or placing cotton in ear.
- Repeat as needed, use when pain reoccurs.

Other information:

Active ingredients are manufactured according to homeopathic principles and are therefore non-toxic and have no known side effects.

Inactive ingredient:

Vegetable Glycerin

Principle Display Panel

Rite Aid Ear Drops
Homeopathic
Earache Remedy
10 ml/ 0.33 fl oz

Rite Aid Earache Box